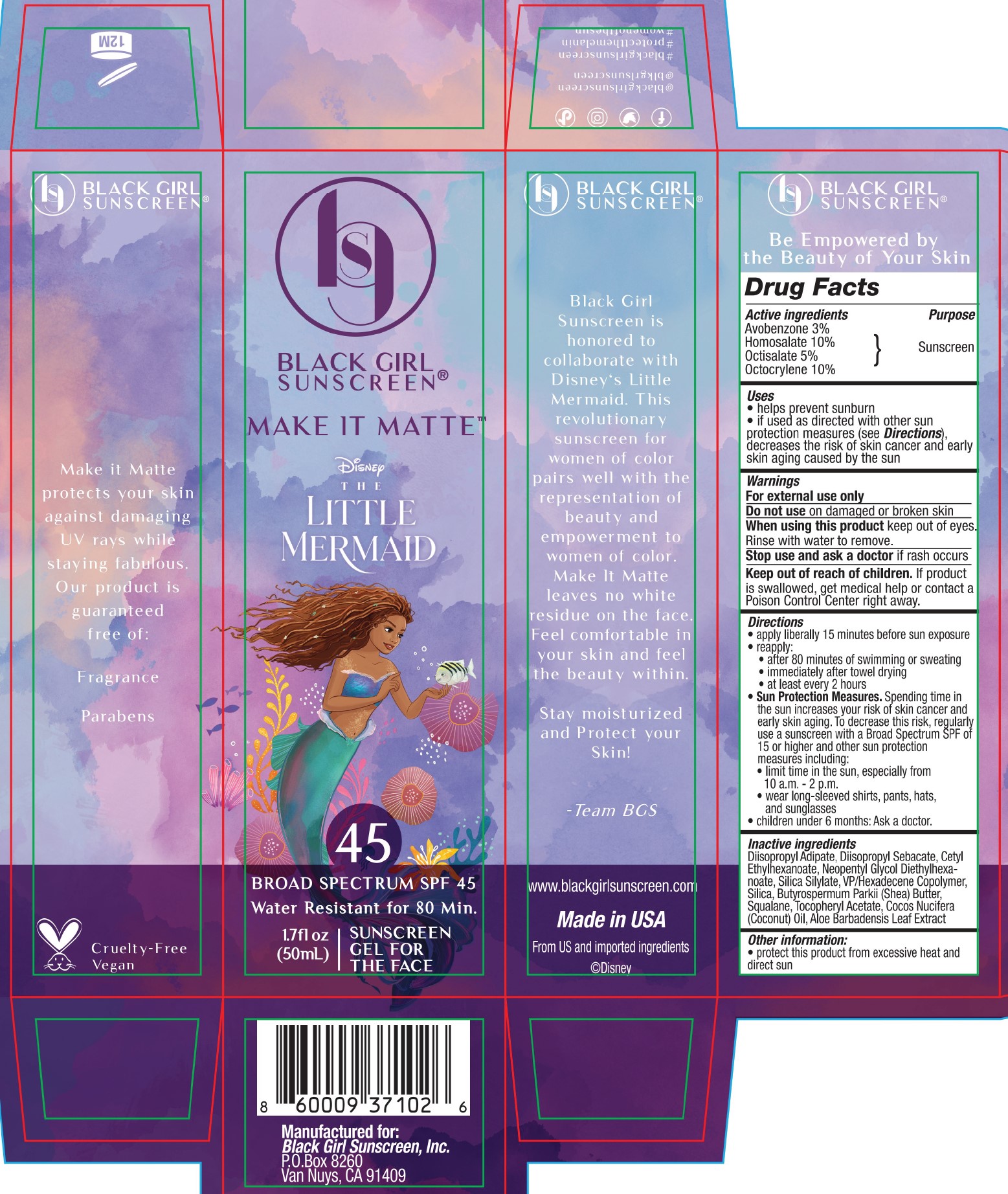 DRUG LABEL: Black Girl Sunscreen
NDC: 84204-0006 | Form: GEL
Manufacturer: Black Girl Sunscreen, LLC
Category: otc | Type: HUMAN OTC DRUG LABEL
Date: 20250115

ACTIVE INGREDIENTS: OCTOCRYLENE 95 mg/1 mL; OCTISALATE 47.5 mg/1 mL; AVOBENZONE 28.5 mg/1 mL; HOMOSALATE 95 mg/1 mL
INACTIVE INGREDIENTS: CETYL ETHYLHEXANOATE; NEOPENTYL GLYCOL DIETHYLHEXANOATE; VINYLPYRROLIDONE/HEXADECENE COPOLYMER; COCONUT OIL; SHEA BUTTER; DIISOPROPYL ADIPATE; DIISOPROPYL SEBACATE; SILICON DIOXIDE; ALPHA-TOCOPHEROL ACETATE; ALOE VERA LEAF; SQUALANE

Black Girl Sunscreen Broad Spectrum SPF 45 Ultra Sheer Sunscreen Gel

Active Ingredients

Avobenzone 3%

Homosalate 10%

Octisalate 5%

Octocrylene 10%

Purpose

Sunscreen

Uses

helps prevent sunburn

if used as directed with other sun protection measures (see Directions), decreases the risk of skin cancer and early skin aging caused by the sun

Warnings

For external use only

Do not use

Do not useon damaged or broken skin

When using this product

When using this productkeep out of eyes. Rinse with water to remove.

Stop use and ask a doctor

Stop use and ask a doctorif rash occurs

Keep out of reach of children.If product is swallowed, get medical help or contact a Poison Control Center right away.

Directions

apply liberally 15 minutes before sun exposure

reapply:

after 80 minutes of swimming or sweating

immediately after towel drying

at least every 2 hours

Sun Protection Measures.Spending time in the sun increases your risk of skin cancer and early skin aging. To decrease this risk, regularly use a sunscreen with a broad spectrum SPF of 15 or higher and other sun protection measures including:

limit time in the sun, especially from 10 a.m. - 2 p.m.

wear long-sleeved shirts, pants, hats and sunglasses

children under 6 months: Ask a doctor.

INACTIVE INGREDIENT

Diisopropyl Adipate, Diisopropyl Sebacate, Cetyl Ethylhexanoate, Neopentyl Glycol Diethylhexanoate, Silica Silylate, VP/Hexadecene Copolymer, Silica, Butryospermum Parkii (Shea) Butter, Squalane, Tocopheryl Acetate, Cocos Nucifera (Coconut) Oil, Aloe Barbadensis Leaf Extract

Other information

Protect this product form excessive heat and direct sun